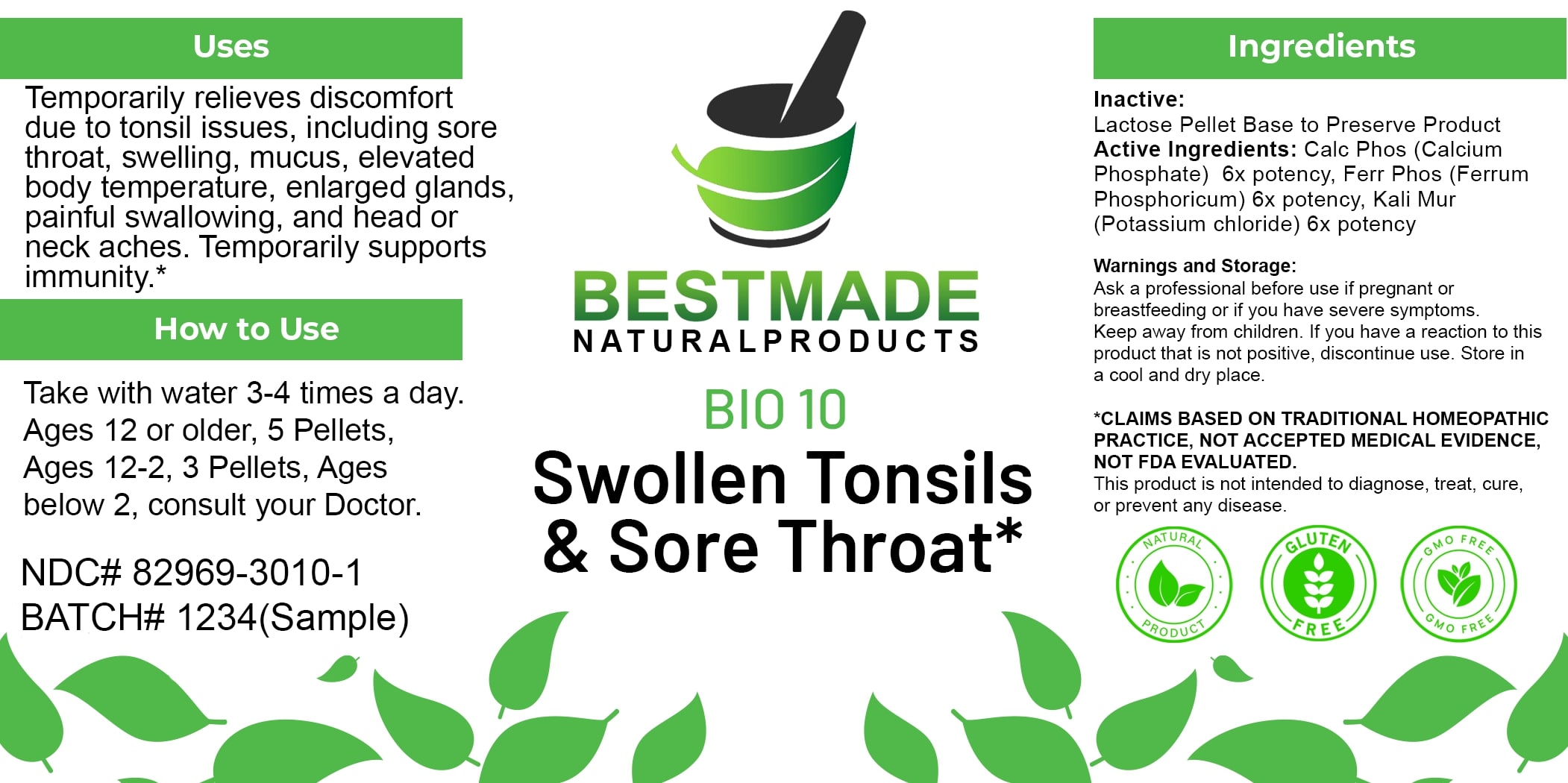 DRUG LABEL: Bestmade Natural Products Bio10
NDC: 82969-3010 | Form: TABLET, SOLUBLE
Manufacturer: Bestmade Natural Products
Category: homeopathic | Type: HUMAN OTC DRUG LABEL
Date: 20250122

ACTIVE INGREDIENTS: CALCIUM PHOSPHATE 6 [hp_X]/6 [hp_X]; FERRIC PYROPHOSPHATE 6 [hp_X]/6 [hp_X]; POTASSIUM CHLORIDE 6 [hp_X]/6 [hp_X]
INACTIVE INGREDIENTS: LACTOSE, UNSPECIFIED FORM 6 [hp_X]/6 [hp_X]

BIO10

DOSAGE AND ADMINISTRATION

How to Use

Take with water 3-4 times a day. Ages 12 or older, 5 Pellets, Ages 12-2, 3 Pellets, Ages below 2, consult your Doctor.

INACTIVE INGREDIENT

Ingredients

Inactive: Lactose Pellet Base to Preserve Product

ACTIVE INGREDIENT

Active Ingredients: Calc Phos (Calcium Phosphate) 6x potency, Ferr Phos (Ferrum Phosphoricum) 6x potency, Kali Mur (Potassium chloride) 6x potency

KEEP OUT OF REACH OF CHILDREN

Warnings and Storage:

Ask a professional before use if pregnant or breastfeeding or if you have severe symptoms. Keep away from children. If you have a reaction to this product that is not positive, discontinue use. Store in a cool and dry place.

Uses

Temporarily relieves discomfort due to tonsil issues, including sore throat, swelling, mucus, elevated body temperature, enlarged glands, painful swallowing, and head or neck aches. Temporarily supports immunity.*

*CLAIMS BASED ON TRADITIONAL HOMEOPATHIC PRACTICE, NOT ACCEPTED MEDICAL EVIDENCE. NOT FDA EVALUATED.

This product is not intended to diagnose, treat, cure, or prevent any disease.

Uses

Temporarily relieves discomfort due to tonsil issues, including sore throat, swelling, mucus, elevated body temperature, enlarged glands, painful swallowing, and head or neck aches. Temporarily supports immunity.*

*CLAIMS BASED ON TRADITIONAL HOMEOPATHIC PRACTICE, NOT ACCEPTED MEDICAL EVIDENCE. NOT FDA EVALUATED.

This product is not intended to diagnose, treat, cure, or prevent any disease.

Warnings and Storage:

Ask a professional before use if pregnant or breastfeeding or if you have severe symptoms. Keep away from children. If you have a reaction to this product that is not positive, discontinue use. Store in a cool and dry place.

*CLAIMS BASED ON TRADITIONAL HOMEOPATHIC PRACTICE, NOT ACCEPTED MEDICAL EVIDENCE. NOT FDA EVALUATED.

This product is not intended to diagnose, treat, cure, or prevent any disease.

Entire package label